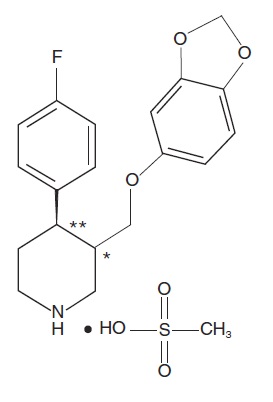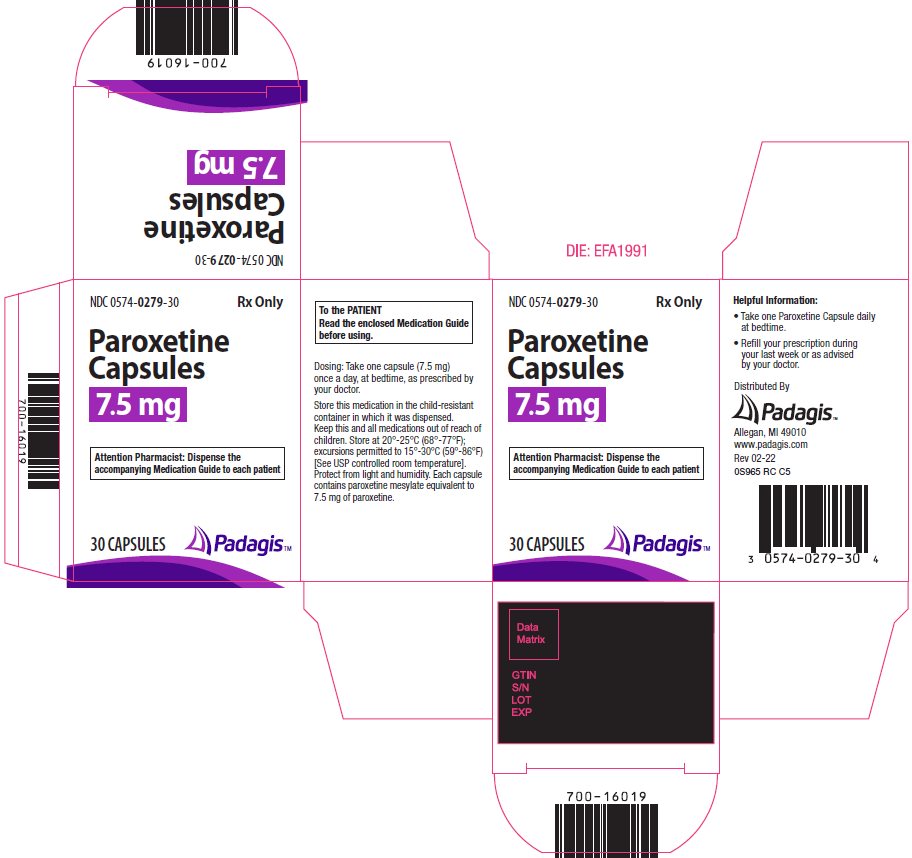 DRUG LABEL: Paroxetine
NDC: 0574-0279 | Form: CAPSULE
Manufacturer: Padagis US LLC
Category: prescription | Type: HUMAN PRESCRIPTION DRUG LABEL
Date: 20230901

ACTIVE INGREDIENTS: PAROXETINE MESYLATE 7.5 mg/1 1
INACTIVE INGREDIENTS: ANHYDROUS DIBASIC CALCIUM PHOSPHATE; MAGNESIUM STEARATE; GELATIN, UNSPECIFIED; TITANIUM DIOXIDE; FD&C YELLOW NO. 6; FD&C RED NO. 3; FD&C RED NO. 40; SHELLAC; FERROSOFERRIC OXIDE

HIGHLIGHTS OF PRESCRIBING INFORMATION

These highlights do not include all the information needed to use PAROXETINE capsules safely and effectively. See full prescribing information for PAROXETINE capsules.
PAROXETINE capsules, for oral use
Initial U.S. Approval: 1992

RECENT MAJOR CHANGES

Warnings and Precautions, Sexual Dysfunction (5.12) 09/2023

WARNING: SUICIDAL THOUGHTS AND BEHAVIORS

See full prescribing information for complete boxed warning.

- Potential for increased risk of suicidal thinking and behavior (5.1)
- Monitor for worsening and emergence of suicidal thoughts and behaviors (5.1)

Monitor for worsening and emergence of suicidal thoughts and behaviors (5.1)

1 INDICATIONS AND USAGE

- Paroxetine capsules are a selective serotonin reuptake inhibitor (SSRI) indicated for the treatment of moderate to severe vasomotor symptoms associated with menopause (VMS) (1) Limitation of Use: Paroxetine capsules are not indicated for the treatment of any psychiatric condition (1)

2 DOSAGE AND ADMINISTRATION

- The recommended dosage of paroxetine capsules is 7.5 mg once daily, at bedtime (2.1)

3 DOSAGE FORMS AND STRENGTHS

- Capsules: 7.5 mg (3)

4 CONTRAINDICATIONS

- Concurrent use with monoamine oxidase inhibitors (MAOI) or use within 14 days of MAOI use (2.2, 4.1, 5.2, 7.3)
- Use with thioridazine (4.2, 7.1)
- Use with pimozide (4.3, 7.1)
- Hypersensitivity to any ingredient in paroxetine capsules (4.4)
- Pregnancy (4.5, 8.1)

5 WARNINGS AND PRECAUTIONS

- Suicidality: Monitor for suicidality or unusual changes in behavior (5.1)
- Serotonin Syndrome: Paroxetine capsules can cause serotonin syndrome with increased risk when co-administered with other serotonergic agents, but also when taken alone. If it occurs, discontinue paroxetine capsules and serotonergic agents and initiate supportive measures (5.2, 7.3)
- Tamoxifen: Efficacy of tamoxifen may be reduced when administered concomitantly with paroxetine capsules (5.3, 7.1)
- Abnormal Bleeding: Caution patients about the risk of bleeding associated with the concomitant use of paroxetine capsules and non-steroidal anti-inflammatory drugs (NSAIDs), aspirin, or other drugs that affect coagulation (5.4, 7.1)
- Angle-Closure Glaucoma: Angle closure glaucoma has occurred in patients who have untreated anatomically narrow angles and who are treated with antidepressants (5.5)
- Hyponatremia: Can occur in association with syndrome of inappropriate antidiuretic hormone secretion (SIADH) (5.6)
- Bone Fracture: Epidemiological studies have reported an association between SSRI treatment and fractures (5.7)
- Activation of Mania/Hypomania: Screen for bipolar disorder and monitor for mania/hypomania (5.8)
- Seizures: Use cautiously in patients with a history of seizures or with conditions that potentially lower the seizure threshold (5.9)
- Akathisia: Can occur, most likely in the first few weeks of treatment (5.10)
- Cognitive and Motor Impairment: May cause impairment; patients should not operate machinery or motor vehicles until certain that paroxetine capsules do not affect them adversely (5.11)
- Sexual Dysfunction: paroxetine capsule use may cause symptoms of sexual dysfunction. (5.12)

6 ADVERSE REACTIONS

- The most common adverse reactions (≥ 2%) reported in clinical trials were:
headache, fatigue, and nausea/vomiting (6.1)

To report SUSPECTED ADVERSE REACTIONS, contact Padagis at 1-866-634-9120 or FDA at 1-800-FDA-1088 or www.fda.gov/medwatch.

7 DRUG INTERACTIONS

Paroxetine is a strong CYP2D6 inhibitor. Co-administration of paroxetine capsules can alter concentrations of other drugs that are metabolized by CYP2D6. Consider potential drug interactions prior to and during therapy (5.3, 7.1, 7.3). See Full Prescribing Information for a list of clinically significant drug interactions (7.1, 7.2, 7.3)

FULL PRESCRIBING INFORMATION

WARNING: SUICIDAL THOUGHTS AND BEHAVIORS

Antidepressants, including selective serotonin reuptake inhibitors (SSRIs), have been shown to increase the risk of suicidal thoughts and behavior in pediatric and young adult patients when used to treat major depressive disorder and other psychiatric disorders. Because paroxetine capsules are an SSRI, monitor patients closely for worsening and for emergence of suicidal thoughts and behaviors. Advise families and caregivers of the need for close observation and communication with the prescriber [see Warnings and Precautions (5.1)].

1 INDICATIONS AND USAGE

Paroxetine Capsules are indicated for the treatment of moderate to severe vasomotor symptoms (VMS) associated with menopause.

Limitation of Use:

Paroxetine capsules are not indicated for the treatment of any psychiatric condition. Paroxetine capsules contain a lower dose of paroxetine than that used to treat depression, obsessive compulsive disorder, panic disorder, generalized anxiety disorder, social anxiety disorder, and post-traumatic stress disorder. The safety and efficacy of this lower dose of paroxetine in paroxetine capsules have not been established for any psychiatric condition. Patients who require paroxetine for treatment of a psychiatric condition should discontinue paroxetine capsules and initiate a paroxetine-containing medication that is indicated for such use.

2 DOSAGE AND ADMINISTRATION

2.1 Dosage Information

The recommended dosage of paroxetine capsules for the treatment of moderate to severe VMS is 7.5 mg once daily, at bedtime, with or without food.

2.2 Use of Paroxetine Capsules Before or After a Monoamine Oxidase Inhibitor (MAOI)

Wait at least 14 days after discontinuation of an MAOI before initiating therapy with paroxetine capsules. Conversely, allow at least 14 days after stopping paroxetine capsules before starting an MAOI [see Contraindications (4.1), Warnings and Precautions (5.2) and Drug Interactions (7.3)].

3 DOSAGE FORMS AND STRENGTHS

Paroxetine capsules are available as 7.5 mg pink capsules printed with black edible ink with “BRISDELLE” and “7.5 mg” on the capsule. Each capsule contains 9.69 mg paroxetine mesylate equivalent to 7.5 mg paroxetine base.

4 CONTRAINDICATIONS

4.1 Monoamine Oxidase Inhibitors

Concomitant use of an MAOI with paroxetine capsules or within 14 days of stopping treatment with paroxetine capsules is contraindicated because of an increased risk of serotonin syndrome. The use of paroxetine capsules within 14 days of stopping an MAOI is also contraindicated [see Dosage and Administration (2.2), Warnings and Precautions (5.2) and Drug Interactions (7.3)].

Starting paroxetine capsules in a patient who is being treated with linezolid or intravenous methylene blue, both of which inhibit monoamine oxidase, is also contraindicated because of an increased risk of serotonin syndrome [see Dosage and Administration (2.2), Warnings and Precautions (5.2) and Drug Interactions (7.3)].

4.2 Thioridazine

Concomitant use of paroxetine capsules with thioridazine is contraindicated, because thioridazine prolongs the QT interval, and paroxetine can increase thioridazine levels [see Drug Interactions (7.1)].

4.3 Pimozide

Concomitant use of paroxetine capsules with pimozide is contraindicated because pimozide prolongs the QT interval, and paroxetine increases pimozide levels [see Drug Interactions (7.1)].

4.4 Hypersensitivity to any Ingredient in Paroxetine Capsules

Paroxetine capsules are contraindicated in patients with a history of hypersensitivity to paroxetine or any of the other ingredients in paroxetine capsules.

4.5 Pregnancy

Menopausal VMS does not occur during pregnancy and paroxetine capsules may cause fetal harm [see Use in Specific Populations (8.1)].

5 WARNINGS AND PRECAUTIONS

5.1 Suicidal Thoughts and Behaviors

Paroxetine capsules are not approved for any psychiatric condition.

Antidepressants, including those that contain an SSRI, increase the risk of suicidal thinking and behavior (suicidality) in pediatric and young adult patients when used to treat major depressive disorder (MDD) and other psychiatric disorders. There is limited information regarding suicidality in women who use paroxetine capsules for treatment of VMS. The paroxetine capsule trials excluded women with a presence or history of previous psychiatric disorders.

Consider discontinuing paroxetine capsules in patients with worsening depression or those who experience emergent suicidality or symptoms that might be precursors to worsening depression or suicidality, especially if these symptoms are severe, abrupt in onset, or were not part of the patient’s presenting symptoms.

All patients being treated with paroxetine capsules should be observed closely for clinical worsening, suicidality, and unusual changes in behavior, especially during the initial few months of treatment.

Anxiety, agitation, panic attacks, insomnia, irritability, hostility, aggressiveness, impulsivity, akathisia (psychomotor restlessness), hypomania, and mania have been reported in patients being treated with antidepressants for MDD as well as for other psychiatric and nonpsychiatric indications. Although a causal link between the emergence of such symptoms and either the worsening of depression and/or the emergence of suicidal impulses has not been established, there is concern that such symptoms may represent precursors to emerging suicidality.

Families and caregivers of patients being treated with paroxetine capsules should be alerted about the need to monitor patients for the emergence of agitation, irritability, unusual changes in behavior, and the other symptoms described above, as well as the emergence of suicidality, and to report such symptoms immediately to healthcare providers.

5.2 Serotonin Syndrome

Paroxetine capsules can precipitate serotonin syndrome, a potentially life-threatening condition. The risk is increased with concomitant use of other serotonergic agents (including triptans, tricyclic antidepressants, fentanyl, tramadol, meperidine, methadone, lithium, tryptophan, buspirone, amphetamines, and St. John’s Wort) and with drugs that impair metabolism of serotonin, i.e., monoamine oxidase inhibitors (MAOIs) [see Contraindications (4), Drug Interactions (7.3)]. Serotonin syndrome can also occur when these drugs are used alone.

Serotonin syndrome symptoms may include mental status changes (e.g., agitation, hallucinations, delirium, and coma), autonomic instability (e.g., tachycardia, labile blood pressure, dizziness, diaphoresis, flushing, hyperthermia), neuromuscular symptoms (e.g., tremor, rigidity, myoclonus, hyperreflexia, incoordination), and/or gastrointestinal symptoms (e.g., nausea, vomiting, diarrhea). Monitor patients for the emergence of serotonin syndrome.

The concomitant use of paroxetine capsules with MAOIs is contraindicated. Do not start paroxetine capsules in a patient who is being treated with MAOIs such as linezolid or intravenous methylene blue. All reports with methylene blue that provided information on the route of administration involved intravenous administration in the dose range of 1 mg/kg to 8 mg/kg. No reports involved the administration of methylene blue by other routes (such as oral tablets or local tissue injection) or at lower doses. There may be circumstances when it is necessary to initiate treatment with an MAOI such as linezolid or intravenous methylene blue in a patient taking paroxetine capsules. Paroxetine capsules should be discontinued before initiating treatment with the MAOI [see Contraindications (4.1) and Dosage and Administration (2.2)].

If concomitant use of paroxetine capsules with other serotonergic drugs (e.g., triptans, tricyclic antidepressants, fentanyl, lithium, tramadol, tryptophan, buspirone, amphetamines, and St. John’s Wort) is clinically warranted, consider the increased risk of serotonin syndrome and carefully observe the patient, particularly during treatment initiation [see Contraindications (4.1) Drug Interactions (7.3)].

Discontinue paroxetine capsules and any concomitant serotonergic agents immediately if the above events occur and initiate supportive symptomatic treatment.

5.3 Potential Impact on Tamoxifen Efficacy

It is uncertain whether the co-administration of paroxetine and tamoxifen has a significant adverse effect on the efficacy of tamoxifen. Some studies have shown that the efficacy of tamoxifen, as measured by the risk of breast cancer relapse/mortality, may be reduced when co-prescribed with paroxetine as a result of paroxetine’s irreversible inhibition of CYP2D6 [see Drug Interactions (7.1)]. However, other studies have failed to demonstrate such a risk. When tamoxifen is used for the treatment or prevention of breast cancer, weigh the likely benefit of paroxetine capsules for treating VMS vs. the risk of possible decreased tamoxifen effectiveness, and consider avoiding the concomitant use of paroxetine capsules for VMS treatment.

5.4 Abnormal Bleeding

SSRIs, including paroxetine capsules, may increase the risk of bleeding events. Concomitant use of aspirin, nonsteroidal anti-inflammatory drugs (NSAIDs), warfarin, and other anticoagulants may add to this risk. Case reports and epidemiological studies (case-control and cohort design) have demonstrated an association between use of drugs that interfere with serotonin reuptake and the occurrence of gastrointestinal bleeding. Bleeding events related to SSRIs have ranged from ecchymosis, hematoma, epistaxis, and petechiae to life-threatening hemorrhages. Caution patients about the risk of bleeding associated with the concomitant use of paroxetine capsules and NSAIDs, aspirin, or other drugs that affect coagulation [see Drug Interactions (7.1)].

5.5 Angle-Closure Glaucoma

The pupillary dilation that occurs following use of many antidepressants and paroxetine capsules may trigger an angle closure attack in a patient with anatomically narrow angles who does not have a patent iridectomy.

5.6 Hyponatremia

Hyponatremia may occur as a result of treatment with SSRIs, including paroxetine capsules. Elderly patients may be at greater risk. In many cases, the hyponatremia appears to be the result of the syndrome of inappropriate antidiuretic hormone secretion (SIADH). Cases with serum sodium lower than 110 mmol/L have been reported in patients using SSRIs. Also, patients taking diuretics or who are volume-depleted can be at greater risk. Consider discontinuation of paroxetine capsules in patients with symptomatic hyponatremia and institute appropriate medical intervention.

Signs and symptoms of hyponatremia include headache, difficulty concentrating, memory impairment, confusion, weakness, and unsteadiness, which can lead to falls. Signs and symptoms associated with more severe and/or acute cases have included hallucination, syncope, seizure, coma, respiratory arrest, and death.

5.7 Bone Fracture

Epidemiological studies on bone fracture risk following exposure to SSRIs have reported an association between SSRI treatment and fractures. It is unknown to what extent fracture risk is directly attributable to SSRI treatment. If a paroxetine capsule-treated patient presents with unexplained bone pain, point tenderness, swelling, or bruising, consider the possibility of a fragility fracture.

5.8 Screening Patients for Bipolar Disorder and Monitoring for Mania/Hypomania

Paroxetine capsules are only indicated for the treatment of moderate to severe VMS and are not approved for use in treating either depression or bipolar depression. However, prior to initiating treatment with paroxetine capsules, all patients should be adequately screened to determine if they are at risk for bipolar disorder; such screening should include a detailed psychiatric history, including a family history of suicide, bipolar disorder, and depression. It is generally believed (though not established in controlled trials) that use of an antidepressant alone may increase the likelihood of precipitation of a mixed/manic episode in patients at risk for bipolar disorder.

5.9 Seizures

In premarketing testing of paroxetine, seizures occurred in 0.1% of paroxetine-treated patients. Use paroxetine capsules cautiously in patients with a history of seizures or with conditions that potentially lower the seizure threshold. Evaluate and consider discontinuing use in any patient who develops seizures.

5.10 Akathisia

The use of paroxetine or other SSRIs has been associated with the development of akathisia, which is characterized by an inner sense of restlessness and psychomotor agitation such as an inability to sit or stand still usually associated with subjective distress. This is most likely to occur within the first few weeks of treatment. Discontinue treatment with paroxetine capsules if akathisia occurs.

5.11 Potential for Cognitive and Motor Impairment

Paroxetine capsules have the potential to impair judgment, thinking, or motor skills. Patients should be cautioned about operating hazardous machinery, including motor vehicles, until they are reasonably certain that the drug treatment does not affect them adversely.

5.12 Sexual Dysfunction

Use of SSRIs, including paroxetine capsules, may cause symptoms of sexual dysfunction. In female patients, SSRI/SNRI use may result in decreased libido and delayed or absent orgasm.

It is important for prescribers to inquire about sexual function prior to initiation of paroxetine capsules and to inquire specifically about changes in sexual function during treatment, because sexual function may not be spontaneously reported. When evaluating changes in sexual function, obtaining a detailed history (including timing of symptom onset) is important because sexual symptoms may have other causes, including the underlying psychiatric disorder. Discuss potential management strategies to support patients in making informed decisions about treatment.

6 ADVERSE REACTIONS

The following serious adverse reactions are discussed elsewhere in labeling:

- Suicidality [see Warnings and Precautions (5.1)]
- Serotonin syndrome [see Warnings and Precautions (5.2)]
- Abnormal bleeding [see Warnings and Precautions (5.4)]
- Angle-Closure Glaucoma [see Warnings and Precautions (5.5)]
- Hyponatremia [see Warnings and Precautions (5.6)]
- Bone Fracture [see Warnings and Precautions (5.7)]
- Mania/Hypomania [see Warnings and Precautions (5.8)]
- Seizure [see Warnings and Precautions (5.9)]
- Akathisia [see Warnings and Precautions (5.10)]

6.1 Clinical Trials Experience

Because clinical trials are conducted under widely varying conditions, adverse reaction rates observed in the clinical trials of a drug cannot directly be compared to rates in the clinical trials of another drug and may not reflect the rates observed in practice.

The data described below reflect exposure to paroxetine capsules in the one 8-week Phase 2 randomized, placebo-controlled trial and the two Phase 3 randomized, placebo-controlled, 12-week and 24-week trials for the treatment of moderate to severe VMS [see Clinical Studies (14)]. In these trials, a total of 635 women were exposed to paroxetine capsules 7.5 mg administered orally once daily and 641 women received placebo. The majority of paroxetine capsule-treated patients were Caucasian (68%) and African American (30%), with a mean age of 55 years (range 40 to 73 years). Women with a history of suicidal ideation or suicidal behavior were excluded from these studies.

Adverse Reactions Leading to Study Discontinuation: A total of 4.7% of women taking paroxetine capsules discontinued from the clinical trials due to an adverse reaction, compared to 3.7% of women on placebo; the most frequent adverse reactions leading to discontinuation among paroxetine-treated women were: abdominal pain (0.3%), attention disturbances (0.3%), headache (0.3%), and suicidal ideation (0.3%).

Common Adverse Reactions: Overall, based on investigators’ determinations about what events were likely to be drug-related, about 20% of women treated with paroxetine capsules reported at least 1 adverse reaction in the three controlled studies. The most common adverse reactions (≥ 2% and more common among paroxetine capsule-treated women) reported in these studies were headache, fatigue/malaise/lethargy, and nausea/vomiting. Of these commonly reported adverse reactions, nausea occurred primarily within the first 4 weeks of treatment and fatigue occurred primarily within the first week of treatment, and decreased in frequency with continued therapy.

The adverse reactions that occurred in at least 2% of patients in the paroxetine capsule group and at a higher incidence than placebo are shown in Table 1 for the pooled Phase 2 and Phase 3 trials.

Table 1 Frequency of Adverse Reactions in the Phase 2 and Phase 3 Trials (≥ 2% and at a higher incidence than placebo)

 | Frequency n (%)
 | Paroxetine Capsules (n = 635) | Placebo (n = 641)
Nervous system disorders
Headache | 40 (6.3) | 31 (4.8)
General disorders and administration site conditions
Fatigue, malaise, lethargy | 31 (4.9) | 18 (2.8)
Gastrointestinal disorders
Nausea, vomiting | 27 (4.3) | 15 (2.3)

Certain symptoms were seen more frequently in women at the time of discontinuation of paroxetine capsules compared to women discontinuing placebo, and have also been reported upon discontinuation of other formulations of paroxetine, particularly when abrupt. These include increased dreaming/nightmares, muscle cramps/spasms/twitching, headache, nervousness/anxiety, fatigue/tiredness, restless feeling in legs, and trouble sleeping/insomnia. While these events are generally self-limiting, there have been reports of serious discontinuation symptoms with other formulations of paroxetine.

Serious Adverse Reactions: In the pooled Phase 2 and Phase 3 trials, three paroxetine capsule-treated patients reported a serious adverse reaction of suicidal ideation and one paroxetine capsule-treated patient reported a serious adverse reaction of suicide attempt. There were no serious adverse reactions of suicidal ideation or suicide attempt reported among the placebo-treated patients.

6.2 Postmarketing Experience

The following adverse reactions have been identified from clinical studies of paroxetine and during post-approval use of other formulations of paroxetine. Because some of these reactions are reported voluntarily from a population of uncertain size, it is not always possible to reliably estimate their frequency or establish a causal relationship to drug exposure.

Blood and Lymphatic System Disorders: Idiopathic thrombocytopenic purpura, Events related to impaired hematopoiesis (including aplastic anemia, pancytopenia, bone marrow aplasia, agranulocytosis).

Cardiac Disorders: Atrial fibrillation, Pulmonary edema, Ventricular fibrillation, Ventricular tachycardia (including torsades de pointes).

Gastrointestinal Disorders: Pancreatitis, Pancreatitis hemorrhagic, Vomiting.

General Disorders and Administration Site Conditions: Death, Drug withdrawal syndrome, Malaise.

Hepatobiliary Disorders: Drug-induced liver injury, Hepatic failure, Jaundice.

Immune System Disorders: Anaphylactoid reaction, Angioedema, Toxic epidermal necrolysis.

Investigations: Elevated liver tests (the most severe cases were deaths due to liver necrosis, and grossly elevated transaminases associated with severe liver dysfunction).

Metabolism and Nutrition Disorders: Diabetes mellitus inadequate control, Type 2 diabetes mellitus.

Nervous System Disorders: Neuroleptic malignant syndrome, Paresthesia, Somnolence, Tremor, Anosmia, Hyposmia.

Psychiatric Disorders: Aggression, Agitation, Anxiety, Confusional state, Depression, Disorientation, Homicidal ideation, Insomnia, Restlessness.

Respiratory, Thoracic and Mediastinal Disorders: Pulmonary hypertension.

Skin and Subcutaneous Tissue Disorders: Hyperhidrosis, Stevens-Johnson syndrome, Drug reaction with eosinophilia and systemic symptoms (DRESS).

7 DRUG INTERACTIONS

No drug-drug interaction studies have been conducted with paroxetine capsules.

7.1 Potential for Paroxetine Capsules to Affect Other Drugs

Paroxetine is a strong CYP2D6 inhibitor. Clinical drug interaction studies have been performed with substrates of CYP2D6 and show that paroxetine can inhibit the metabolism of drugs metabolized by CYP2D6 [see Clinical Pharmacology (12.3)]. Table 2 contains examples of drugs with a metabolism that may be affected by co-administration with paroxetine capsules.

Table 2 Effects of Paroxetine on Other Drugs

Concomitant Drug Name | Effect of Paroxetine on Other Drugs | Clinical Recommendations
Thioridazine | Increased plasma concentrations of thioridazine; Potential QTc prolongation | Concomitant use of thioridazine and paroxetine capsules is contraindicated.
Pimozide | Increased plasma concentrations of pimozide.; Potential QTc prolongation | Concomitant use of pimozide and paroxetine capsules is contraindicated.
Tamoxifen | Reduced plasma concentrations of active tamoxifen metabolite | Consider avoiding concomitant use of tamoxifen and paroxetine capsules.
Tricyclic Antidepressants (TCA) (e.g., Desipramine) | Increased plasma concentrations and elimination half-life | Plasma TCA concentrations may need to be monitored and the dose of TCA may need to be reduced if a TCA is co-administered with paroxetine capsules. Monitor tolerability.
Risperidone | Increased plasma concentrations of risperidone | A lower dosage of risperidone may be necessary (see the Full Prescribing Information for risperidone). Monitor tolerability.
Atomoxetine | Increased exposure of atomoxetine | A lower dosage of atomoxetine may be necessary (see Full Prescribing Information for atomoxetine). Monitor tolerability.
Drugs Highly Bound to Plasma Protein (e.g., Warfarin) | Increased free plasma concentrations | The dosage of warfarin may need to be reduced. Monitor tolerability and the International Normalized Ratio.
Digoxin | Decreased plasma concentrations of digoxin | Dosage of digoxin may need to be increased. Monitor digoxin concentrations and clinical effect.
Theophylline | Increased plasma concentrations of theophylline | Dosage of theophylline may need to be decreased. Monitor theophylline concentrations and tolerability.

Use caution if co-administering paroxetine capsules with other drugs that are metabolized by CYP2D6, including nortriptyline, amitriptyline, imipramine, desipramine, fluoxetine, phenothiazines, risperidone, and Type 1C antiarrhythmics (e.g., propafenone, flecainide, and encainide).

7.2 Potential for Other Drugs to Affect Paroxetine Capsules

The metabolism and pharmacokinetics of paroxetine may be affected by the induction and inhibition of drug metabolizing enzymes such as CYP2D6. Table 3 contains a list of drugs that may affect the pharmacokinetics of paroxetine capsules when administered concomitantly [see Clinical Pharmacology (12.3)].

Table 3 Effects of Other Drugs on Paroxetine

Concomitant Drug Name | Effect of Concomitant Drug on Paroxetine | Clinical Recommendations
Phenobarbital | Decreased paroxetine exposure | No dose adjustment for paroxetine capsules.; Monitor clinical effect of paroxetine capsules.
Phenytoin | Decreased paroxetine exposure | No dose adjustment for paroxetine capsules.; Monitor clinical effect of paroxetine capsules.
Fosamprenavir/Ritonavir | Decreased plasma concentration of paroxetine | No dose adjustment for paroxetine capsules.; Monitor clinical effect of paroxetine capsules.
Cimetidine | Increased plasma concentration of paroxetine | No dose adjustment for paroxetine capsules.; Monitor clinical effect of paroxetine capsules.

Use caution if co-administering paroxetine capsules with other drugs that inhibit CYP2D6 (e.g., quinidine).

7.3 Other Potentially Significant Drug Interactions

Monoamine Oxidase Inhibitors (MAOIs)

Serious adverse reactions such as serotonin syndrome have been reported in patients receiving a concomitant SSRI and MAOI, in patients started on an SSRI who recently received an MAOI and in patients started on an MAOI who recently received an SSRI. Therefore, concomitant use of MAOIs with paroxetine capsules or use of paroxetine capsules and an MAOI within 14 days of each other is contraindicated [see Dosage and Administration (2.2), Contraindications (4.1) and Warnings and Precautions (5.2)].

Serotonergic Drugs

If concomitant use of paroxetine capsules with other serotonergic drugs (e.g., other SNRIs, SSRIs, triptans, tricyclic antidepressants, opioids, lithium, tryptophan, buspirone, amphetamines, and St. John’s Wort) is clinically warranted, consider the increased risk of serotonin syndrome and carefully observe the patient, particularly during treatment initiation [see Warnings and Precautions (5.2)]. An interaction between paroxetine and tryptophan may occur when they are co-administered. Adverse experiences, consisting primarily of headache, nausea, sweating, and dizziness, have been reported when tryptophan was administered to patients taking paroxetine. Consequently, concomitant use of paroxetine capsules with tryptophan is not recommended.

Drugs that Interfere with Hemostasis (e.g., NSAIDs, Aspirin, and Warfarin)

Altered anticoagulant effects, including increased bleeding, have been reported when SSRIs are co-administered with NSAIDs, aspirin, and warfarin or other drugs that affect coagulation. There may be a pharmacodynamic interaction between paroxetine and warfarin that causes an increased bleeding diathesis despite unaltered prothrombin time. Carefully monitor patients receiving warfarin therapy when paroxetine capsules is initiated or discontinued [see Warnings and Precautions (5.4)].

8 USE IN SPECIFIC POPULATIONS

8.1 Pregnancy

Pregnancy Category X

Risk Summary

Paroxetine capsules are contraindicated in pregnant women because menopausal VMS does not occur during pregnancy and paroxetine can cause fetal harm. Epidemiological studies have shown that infants exposed to paroxetine in the first trimester of pregnancy may have an increased risk of cardiovascular malformations. Cardiac malformations are a common congenital abnormality. These data would suggest that the risk of a cardiac abnormality following paroxetine exposure in the first trimester may increase the risk from 1% to 2%. Exposure to SSRIs in late pregnancy may lead to an increased risk for neonatal complications requiring prolonged hospitalization, respiratory support, and tube feeding, and/or persistent pulmonary hypertension of the newborn (PPHN). No teratogenicity was seen in reproductive development studies conducted in rats and rabbits. However, an increase in rat pup deaths was seen during the first 4 days of lactation when dosing occurred during the last trimester of gestation and continued throughout lactation, at a dose approximately equal to the maximum recommended human dose (MRHD) for VMS (7.5 mg) on an mg/m^2 basis. If this drug is used during pregnancy, or if the patient becomes pregnant while taking this drug, the patient should be apprised of the potential hazard to a fetus.

Human Data

First-Trimester Pregnancy Exposure

- Epidemiologic studies which include data from the Swedish National Registry, a retrospective cohort study using United Healthcare data and a meta-analysis of studies (1992-2008) have shown a less than 2-fold increased risk of cardiac malformations, primarily ventricular septal and atrial septal defects, with first-trimester paroxetine exposure. Two case-control studies using separate databases with > 9000 birth defect cases and > 4000 controls showed 7 and 6 paroxetine-exposed infants respectively, with right ventricular outflow tract obstructions, a 2- to 3-fold increased risk. An increase in overall congenital malformations with first-trimester paroxetine use was not observed in all studies.

Third-Trimester Pregnancy Exposure

- Neonates exposed to SSRIs late in the third trimester have developed complications requiring prolonged hospitalization, respiratory support, and tube feeding. Such complications can arise immediately upon delivery. Reported clinical findings have included respiratory distress, cyanosis, apnea, seizures, temperature instability, feeding difficulty, vomiting, hypoglycemia, hypotonia, hypertonia, hyperreflexia, tremor, jitteriness, irritability, and constant crying. These features are consistent with either a direct toxic effect of SSRIs or, possibly, a drug discontinuation syndrome. It should be noted that in some cases, the clinical picture is consistent with serotonin syndrome [see Warnings and Precautions (5.2)].
- Infants exposed to SSRIs in late pregnancy may have an increased risk for persistent pulmonary hypertension of the newborn (PPHN). PPHN occurs in 1 – 2 per 1000 live births in the general population and is associated with substantial neonatal morbidity and mortality. In a retrospective case-control study of 377 women whose infants were born with PPHN and 836 women whose infants were born healthy, the risk for developing PPHN was approximately 6-fold higher for infants exposed to SSRIs after the 20th week of gestation compared to infants who had not been exposed to antidepressants during pregnancy. There is currently no corroborative evidence regarding the risk for PPHN following exposure to SSRIs in pregnancy; this is the first study that has investigated the potential risk. The study did not include enough cases with exposure to individual SSRIs to determine if all SSRIs posed similar levels of PPHN risk.

Animal Data

Reproduction studies were performed at doses up to 50 mg/kg/day in rats and 6 mg/kg/day in rabbits administered during organogenesis. These doses are approximately 65 (rat) and 16 (rabbit) times the maximum recommended human dose (MRHD) for VMS on an mg/m^2 basis. There were no teratogenic effects. However, in rats, there was an increase in pup deaths during the first 4 days of lactation when dosing occurred during the last trimester of gestation and continued throughout lactation. This effect occurred at a dose of 1 mg/kg/day or approximately equal to the MRHD for VMS on an mg/m^2 basis. The no-effect dose for rat pup mortality was not determined. The cause of these deaths is unknown.

8.3 Nursing Mothers

Paroxetine is excreted in human milk. Because of the potential for serious adverse reactions in nursing infants from paroxetine capsules, a decision should be made whether to discontinue nursing or to discontinue the drug, taking into account the importance of the drug to the mother.

8.4 Pediatric Use

Safety and effectiveness in pediatric patients have not been established; paroxetine capsules are not indicated in the pediatric population.

8.5 Geriatric Use

Clinical studies of paroxetine capsules did not include sufficient numbers of subjects aged 65 and over to determine whether they respond differently from younger subjects. Elderly patients may have elevated paroxetine plasma concentrations compared to younger patients. However, no paroxetine capsules dose adjustment is considered necessary in elderly patients [see Clinical Pharmacology (12.3)].

SSRIs have been associated with cases of clinically significant hyponatremia in elderly patients, who may be at greater risk for this adverse event [see Warnings and Precautions (5.6)].

8.6 Renal Impairment

No paroxetine capsules dose adjustment is considered necessary in patients with renal impairment [see Clinical Pharmacology (12.3)].

8.7 Hepatic Impairment

No paroxetine capsules dose adjustment is considered necessary in patients with liver impairment [see Clinical Pharmacology (12.3)].

10 OVERDOSAGE

The following have been reported with paroxetine tablet overdosage:

- Seizures, which may be delayed, and altered mental status including coma.
- Cardiovascular toxicity, which may be delayed, including QRS and QTc interval prolongation. Hypertension most commonly seen, but rarely can see hypotension alone or with co-ingestants including alcohol.
- Serotonin syndrome (patients with a multiple drug overdosage with other pro-serotonergic drugs may have a higher risk).

Gastrointestinal decontamination with activated charcoal should be considered in patients who present early after a paroxetine overdose.

Consider contacting a poison center (1-800-221-2222) or a medical toxicologist for overdose management recommendations.

11 DESCRIPTION

Paroxetine is an orally administered selective serotonin reuptake inhibitor (SSRI) for the treatment of moderate to severe VMS associated with menopause. It is identified chemically as (-)-trans -4R- (4’-fluorophenyl) - 3S - [(3’,4’-methylenedioxyphenoxy) methyl] piperidine mesylate and has the empirical formula of C19H20FNO3•CH3SO3H.

The molecular weight is 425.5 (329.4 as free base). The structural formula is:

The mesylate salt of paroxetine is an odorless, off-white powder, having a melting point range of 147° to 150°C and a solubility of more than 1 g/mL in water.

Each pink capsule contains 9.69 mg paroxetine mesylate equivalent to 7.5 mg paroxetine base.

Inactive ingredients consist of: dibasic calcium phosphate, sodium starch glycolate, magnesium stearate, gelatin, titanium dioxide, FD&C Yellow #6, FD&C Red #3, FD&C Red #40, shellac, and black iron oxide.

12 CLINICAL PHARMACOLOGY

12.1 Mechanism of Action

Nonclinical studies have shown that paroxetine is an SSRI. Paroxetine capsules are not an estrogen, and its mechanism of action for the treatment of VMS is unknown.

12.2 Pharmacodynamics

Studies at clinically relevant doses in humans have demonstrated that paroxetine blocks the uptake of serotonin into human platelets. In vitro studies in animals also suggest that paroxetine is a selective inhibitor of neuronal serotonin reuptake and has weak effects on norepinephrine and dopamine neuronal reuptake. In vitro radioligand binding studies indicate that paroxetine has little affinity for muscarinic alpha1-, alpha2-, beta-adrenergic-, dopamine (D2)-, 5-HT1-, 5-HT2-, and histamine (H1)-receptors.

12.3 Pharmacokinetics

Absorption, Distribution, Metabolism and Excretion

Absorption

Paroxetine is completely absorbed after oral dosing of the mesylate salt. In a study in which healthy postmenopausal women (n=24) received paroxetine 7.5 mg capsules as a daily dose for 14 days, steady-state paroxetine concentrations were achieved by approximately 12 days of dosing for most subjects, although it may take substantially longer in an occasional patient. Peak concentrations were reached at a median of 6 hours (3 to 8 hours range). Steady-state mean values of Cmax, Cmin, and AUC0-last were 13.10 ng/mL (CV 91%), 7.17 ng/mL (CV 99%), and 237 hr*ng/mL (CV 94%), respectively.

Steady-state AUC0-24 values were about 3 times those of AUC0-inf following a single dose, indicating non-linear pharmacokinetics. Steady-state Cmax values were approximately 5 times greater than those attained after a single dose and steady-state exposure based on AUC0-24 was about 10 times greater than AUC0-24 after a single dose.

The nonlinear kinetics and excess accumulation are due to the fact that CYP2D6, an enzyme that is in part responsible for paroxetine metabolism, is readily saturable.

The effects of food on the bioavailability of paroxetine were studied with paroxetine tablets at higher strength. AUC was only slightly increased (6%) when drug was administered with food but the Cmax was 29% greater, while the time to reach peak plasma concentration decreased from 6.4 hours post-dosing to 4.9 hours. Paroxetine capsules can be taken with or without food.

Distribution

Paroxetine distributes throughout the body, including the central nervous system, with only 1% remaining in the plasma.

Approximately 95% and 93% of paroxetine is bound to plasma protein at 100 ng/mL and 400 ng/mL, respectively. Under clinical conditions, paroxetine concentrations would normally be less than 100 ng/mL. Paroxetine does not alter the in vitro protein binding of phenytoin or warfarin.

Metabolism

Paroxetine is extensively metabolized after oral administration. The principal metabolites are polar and conjugated products of oxidation and methylation, which are readily cleared. Conjugates with glucuronic acid and sulfate predominate, and major metabolites have been isolated and identified. Data indicate that the metabolites have no more than 1/50 the potency of the parent compound at inhibiting serotonin uptake. The metabolism of paroxetine is accomplished in part by cytochrome CYP2D6. Saturation of this enzyme at clinical doses appears to account for the nonlinearity of paroxetine kinetics with increasing dose and increasing duration of treatment. The role of this enzyme in paroxetine metabolism also suggests potential drug-drug interactions [see Drug Interactions (7)]. At steady state, when the CYP2D6 pathway is essentially saturated, paroxetine clearance is governed by alternative P450 isozymes, which, unlike CYP2D6, show no evidence of saturation.

Excretion

Approximately 64% of a 30 mg oral solution of paroxetine was excreted in the urine with 2% as the parent compound and 62% as metabolites over a 10-day post-dosing period. About 36% of the dose was excreted in the feces (probably via the bile), mostly as metabolites and less than 1% as the parent compound over the 10-day post-dosing period.

Specific Populations

Renal and Liver Impairment

Increased plasma concentrations of paroxetine occur in subjects with renal and hepatic impairment. The mean plasma concentration in patients with creatinine clearance below 30 mL/min was approximately 4 times greater than seen in normal volunteers. Patients with creatinine clearance of 30 to 60 mL/min and patients with hepatic impairment had about a 2-fold increase in plasma concentrations (AUC, Cmax). No paroxetine capsules dose adjustment is considered necessary in patients with renal or hepatic impairment.

Elderly Patients

In a multiple-dose study in the elderly at daily paroxetine doses of 20, 30, and 40 mg, Cmin concentrations were about 70% to 80% greater than the respective Cmin concentrations in nonelderly subjects. No paroxetine capsules dose adjustment is considered necessary in elderly patients.

Drug Interaction Studies

Potential Effect of Paroxetine Capsules on Other Drugs

Drugs Metabolized by CYP3A4

An in vivo drug interaction study involving the co-administration under steady-state conditions of paroxetine and terfenadine, a substrate for cytochrome CYP3A4, revealed no effect of paroxetine on terfenadine pharmacokinetics. In vitro studies have shown ketoconazole, a potent inhibitor of CYP3A4 activity, to be at least 100 times more potent than paroxetine as an inhibitor of the metabolism of several substrates for CYP3A4, including astemizole, triazolam, and cyclosporine. Based on the assumption that the relationship between paroxetine’s in vitro Ki and its lack of effect on terfenadine’s in vivo clearance predicts its effect on other CYP3A4 substrates, paroxetine’s extent of inhibition of CYP3A4 activity is not likely to be of clinical significance.

Drugs Metabolized by CYP2D6

Many drugs are metabolized by the cytochrome P450 isozyme CYP2D6. Like other agents that are metabolized by CYP2D6, paroxetine may significantly inhibit the activity of this isozyme. In most patients (> 90%), this CYP2D6 isozyme is saturated early during paroxetine dosing.

Specific studies investigating the effect of paroxetine on drugs metabolized by CYP2D6 are listed below:

Pimozide: Higher doses of paroxetine have been shown to elevate plasma levels of pimozide. In a controlled study of healthy volunteers, after paroxetine was titrated to 60 mg daily, co-administration of a single dose of 2 mg pimozide was associated with mean increases in pimozide AUC of 151% and Cmax of 62%, compared to pimozide administered alone [see Drug Interactions (7.1)].

Tamoxifen: It is uncertain whether the co-administration of paroxetine and tamoxifen has a significant adverse effect on the efficacy of tamoxifen. Some studies have shown that the efficacy of tamoxifen, as measured by the risk of breast cancer relapse/mortality, may be reduced when co-prescribed with paroxetine as a result of paroxetine’s irreversible inhibition of CYP2D6. However, other studies have failed to demonstrate such a risk [see Warnings and Precautions (5.3) and Drug Interactions (7.1)].

Desipramine: In one study, daily dosing of paroxetine (20 mg once daily) under steady-state conditions increased single dose desipramine (100 mg) Cmax, AUC, and T1/2 by an average of approximately 2-, 5-, and 3-fold, respectively [see Drug Interactions (7.1)].

Risperidone: Daily dosing of paroxetine 20 mg in patients stabilized on risperidone (4 to 8 mg/day), a CYP2D6 substrate, increased mean plasma concentrations of risperidone approximately 4-fold, decreased 9-hydroxyrisperidone concentrations approximately 10%, and increased concentrations of the active moiety (the sum of risperidone plus 9-hydroxyrisperidone) approximately 1.4-fold [see Drug Interactions (7.1)].

Atomoxetine: The effect of paroxetine on the pharmacokinetics of atomoxetine has been evaluated when both drugs were at steady state. In healthy volunteers who were extensive metabolizers of CYP2D6, paroxetine 20 mg daily was given in combination with 20 mg atomoxetine every 12 hours. This resulted in increases in steady-state atomoxetine AUC values that were 6- to 8-fold greater and in atomoxetine Cmax values that were 3- to 4-fold greater than when atomoxetine was given alone [see Drug Interactions (7.1)].

Digoxin: Mean digoxin AUC at steady state decreased by 15% in the presence of paroxetine [see Drug Interactions (7.1)].

Beta Blockers: In a study in which propranolol (80 mg twice daily) was dosed orally for 18 days, the steady-state plasma concentrations of propranolol were unaltered during co-administration with paroxetine (30 mg once daily) for the final 10 days. The effects of propranolol on paroxetine have not been evaluated.

Potential Effect of Other Drugs on Paroxetine Capsules

Concomitant use of paroxetine with other drugs that alter CYP enzymes activities including CYP2D6 may affect the plasma concentrations of paroxetine. Specific studies investigating the effect of other drugs on paroxetine are listed below:

Cimetidine: Cimetidine inhibits many cytochrome P450 enzymes. In a study in which paroxetine (30 mg once daily) was dosed orally for 4 weeks, steady-state plasma concentrations of paroxetine were increased by approximately 50% during co-administration with oral cimetidine (300 mg three times daily) for the final week [see Drug Interactions (7.2)].

Phenobarbital: Phenobarbital induces many cytochrome P450 enzymes. When a single oral 30 mg dose of paroxetine was administered at phenobarbital steady state (100 mg once daily for 14 days), paroxetine AUC and T1/2 were reduced (by an average of 25% and 38%, respectively) compared to paroxetine administered alone. The effect of paroxetine on phenobarbital pharmacokinetics was not studied. Because paroxetine exhibits nonlinear pharmacokinetics, the results of this study may not address the case where the 2 drugs are both being chronically dosed [see Drug Interactions (7.2)].

Phenytoin: When a single oral 30 mg dose of paroxetine was administered at phenytoin steady state (300 mg once daily for 14 days), paroxetine AUC and T1/2 were reduced (by an average of 50% and 35%, respectively) compared to paroxetine administered alone. In a separate study, when a single oral 300 mg dose of phenytoin was administered at paroxetine steady state (30 mg once daily for 14 days), phenytoin AUC was slightly reduced (12% on average) compared to phenytoin administered alone. Because both drugs exhibit nonlinear pharmacokinetics, the above studies may not address the case where the 2 drugs are both being chronically dosed [see Drug Interactions (7.2)].

Digoxin: A clinical drug interaction study showed that concurrent use of digoxin did not affect paroxetine exposure.

Diazepam: A clinical drug interaction study showed that concurrent use of diazepam did not affect paroxetine exposure.

13 NONCLINICAL TOXICOLOGY

13.1 Carcinogenesis, Mutagenesis, Impairment of Fertility

Carcinogenesis

Two-year carcinogenicity studies were conducted in rodents given paroxetine in the diet at 1, 5, and 25 mg/kg/day (mice) and 1, 5, and 20 mg/kg/day (rats). The doses used in these carcinogenicity studies were approximately 16 (mouse) and 26 (rat) times the MHRD for VMS. There was a significantly greater number of male rats in the high-dose group with reticulum cell sarcomas (1/100, 0/50, 0/50, and 4/50 for control, low-, middle-, and high-dose groups, respectively) and a significantly increased linear trend across groups for the occurrence of lymphoreticular tumors in male rats. Female rats were not affected. Although there was a dose-related increase in the number of tumors in mice, there was no drug-related increase in the number of mice with tumors. The relevance of these findings to humans is unknown.

Mutagenesis

Paroxetine produced no genotoxic effect in a battery of 5 in vitro and 2 in vivo assays that included the following: bacterial mutation assay, mouse lymphoma mutation assay, unscheduled DNA synthesis assay, and tests for cytogenetic aberrations in vivo in mouse bone marrow and in vitro in human lymphocytes and in a dominant lethal test in rats.

Impairment of Fertility

A reduced pregnancy rate was found in reproduction studies in rats at a paroxetine dose of 15 mg/kg/day, which is 19 times the MRHD for VMS on an mg/m^2 basis. Irreversible lesions occurred in the reproductive tract of male rats after dosing in toxicity studies for 2 to 52 weeks. These lesions consisted of vacuolation of epididymal tubular epithelium at 50 mg/kg/day and atrophic changes in the seminiferous tubules of the testes with arrested spermatogenesis at 25 mg/kg/day (65 times and 32 times the MHRD for VMS on an mg/m^2 basis, respectively).

14 CLINICAL STUDIES

The efficacy of paroxetine capsules as a treatment for moderate to severe VMS associated with menopause was established in two Phase 3 studies (at a dose of 7.5 mg once daily at bedtime) in 1174 postmenopausal women with a minimum of 7-8 moderate to severe vasomotor symptoms per day at baseline (≥ 50 per week) for 30 days prior to receiving study drug.

Study 1 was a 12-week, randomized, double-blind, placebo-controlled clinical trial with a total of 606 postmenopausal women (average age 55 years, 65% Caucasian and 33% African American, 18% surgically menopausal and 82% naturally menopausal).

Study 2 was a 24-week, randomized, double-blind, placebo-controlled clinical trial with a total of 568 postmenopausal women (average age 54 years, 76% Caucasian and 22% African American, 20% surgically menopausal and 81% naturally menopausal).

The co-primary efficacy endpoints for both studies were the reduction from baseline in VMS frequency and severity at Weeks 4 and 12. Data from Study 1 showed a statistically significant reduction from baseline in the frequency of moderate to severe vasomotor symptoms at Week 4 and Week 12 and a statistically significant reduction in the severity of moderate to severe VMS at Week 4 for paroxetine capsules compared to placebo (Table 4). Data from Study 2 showed a statistically significant reduction from baseline in the frequency and severity of moderate to severe vasomotor symptoms at Week 4 and Week 12 for paroxetine capsules compared to placebo (Table 5).

Table 4

Study 1: Changes in the Daily Frequency and Daily Severity of Moderate to Severe VMS at Weeks 4 and 12 (MITT Population)

 | Frequency |  | Severity
 | Paroxetine Capsules | Placebo | Paroxetine Capsules | Placebo
Baseline
n; Median | 301; 10.4 | 305; 10.4 | 301; 2.5 | 305; 2.5
Change from baseline at Week 4
n; Median; Treatment Difference*; P-value# | 289; -4.3; -1.2; <0.01 | 293; -3.1 | 281; -0.05; -0.05; <0.01 | 289; 0.00
Change from baseline at Week 12
n; Median; Treatment Difference*; P-value# | 264; -5.9; -0.9; <0.01 | 274; -5.0 | 236; -0.06; -0.04; 0.17 | 253; -0.02

MITT population: all consented and randomized subjects with valid baseline daily hot flash diary data who had taken at least 1 dose of study medication and had at least 1 day of on-treatment daily hot flash diary data.

* Treatment Difference: the difference between the median changes from baseline.

# P-value is obtained from rank-ANCOVA model.

Table 5

Study 2: Changes in the Daily Frequency and Daily Severity of Moderate to Severe VMS at Weeks 4 and 12 (MITT Population)

 | Frequency |  | Severity
 | Paroxetine Capsules | Placebo | Paroxetine Capsules | Placebo
Baseline
n; Median | 284; 9.9 | 284; 9.6 | 284; 2.5 | 284; 2.5
Change from baseline at Week 4
n; Median; Treatment Difference*; P-value# | 276; -3.8; -1.3; <0.01 | 274; -2.5 | 268; -0.04; -0.03; 0.04 | 271; -0.01
Change from baseline at Week 12
n; Median; Treatment Difference*; P-value# | 257; -5.6; -1.7; <0.01 | 244; -3.9 | 245; -0.05; -0.05; <0.01 | 236; 0.00

MITT population: all consented and randomized subjects with valid baseline daily hot flash diary data who had taken at least 1 dose of study medication and had at least 1 day of on-treatment daily hot flash diary data.

* Treatment Difference: the difference between the median changes from baseline.

# P-value is obtained from rank-ANCOVA model.

Persistence of benefit at 24 weeks in Study 2 was evaluated with a responder analysis where responders were defined as those patients who achieved ≥ 50% reduction from baseline in the frequency of moderate to severe VMS at Week 24. The proportion of patients achieving a ≥ 50% reduction in the frequency of moderate to severe VMS from baseline to Week 24 was 48% in the paroxetine capsules group and 36% in the placebo group at Week 24.

16 HOW SUPPLIED/STORAGE AND HANDLING

Paroxetine capsules are available as 7.5 mg pink capsules printed with black edible ink with “BRISDELLE” and “7.5 mg” on each capsule.

NDC 0574-0279-30, 30 count bottle

Store at 20°-25°C (68°-77°F); excursions permitted to 15°-30°C (59°-86°F). Protect from light and humidity.

17 PATIENT COUNSELING INFORMATION

See FDA-approved patient labeling (Medication Guide).

Instruct patients to read the Medication Guide before starting therapy with paroxetine capsules and to reread it each time the prescription is renewed.

- Advise patients, their families, and their caregivers to look for the emergence of suicidality, especially early during treatment [see Boxed Warning and Warnings and Precautions (5.1)].
- Instruct patients not to take paroxetine capsules with an MAOI or within 14 days of stopping an MAOI and allow 14 days after stopping paroxetine capsules before starting an MAOI [see Dosage and Administration (2.2) and Contraindications (4.1)].
- Advise patients not to take paroxetine capsules with thioridazine or pimozide [see Contraindications (4.2 and 4.3)].
- Caution patients about the risk of serotonin syndrome, particularly with the concomitant use of paroxetine capsules with triptans, tricyclic antidepressants, opioids, linezolid, tramadol, amphetamines, St. John’s Wort, lithium, tryptophan supplements, other serotonergic agents, or antipsychotic drugs [see Warnings and Precautions (5.2) and Drug Interactions (7.3)]. Instruct patients to contact their health care provider, or report to the emergency room, should they experience signs or symptoms of serotonin syndrome.
- Caution patients that efficacy of tamoxifen may be reduced when administered concomitantly and counsel them about the likely benefit of paroxetine for treating VMS vs. the risk of possible decreased tamoxifen effectiveness [see Warnings and Precautions (5.3)].
- Caution patients about the concomitant use of paroxetine capsules and NSAIDs, aspirin, warfarin, and other anticoagulants because combined use of drugs that interfere with serotonin reuptake has been associated with an increased risk of bleeding [see Warnings and Precautions (5.4)].
- Advise patients that taking paroxetine capsules can cause mild pupillary dilation, which in susceptible individuals, can lead to an episode of angle-closure glaucoma. Pre-existing glaucoma is almost always open-angle glaucoma because angle-closure glaucoma, when diagnosed, can be treated definitively with iridectomy. Open-angle glaucoma is not a risk factor for angle-closure glaucoma. Patients may wish to be examined to determine whether they are susceptible to angle closure, and have a prophylactic procedure (e.g., iridectomy), if they are susceptible [See Warnings and Precautions (5.5)].
- Caution patients about the risk of hyponatremia, particularly elderly patients and those who are taking diuretics or are volume-depleted [see Warnings and Precautions (5.6)].
- Inform patients that there is the possibility for an increased risk of fracture [see Warnings and Precautions (5.7)].
- Advise patients, their families, and their caregivers to observe for signs of activation of mania/hypomania [see Warnings and Precautions (5.8)].
- Advise patients to notify their physician if they become pregnant during therapy [see Contraindications (4.5) and Use in Specific Populations (8.1)]. Caution patients about operating hazardous machinery, including motor vehicles, until they are reasonably certain that paroxetine therapy does not affect their ability to engage in such activities [see Warnings and Precautions (5.11)].
- Advise patients to inform their healthcare provider if they are taking, or plan to take, any prescription or over-the-counter drugs, including herbal supplements, because there is a potential for interaction with paroxetine [see Drug Interactions (7.3)].
- Advise patients that paroxetine, the active ingredient in paroxetine capsules, is also the active ingredient in certain other drugs and these medications should not be taken concomitantly [see Indications and Usage (1) and Drug Interactions (7.3)].
- Advise patients that use of paroxetine capsules may cause symptoms of sexual dysfunction in female patients. Inform patients that they should discuss any changes in sexual function and potential management strategies with their healthcare provider [see Warnings and Precautions (5.12)].

BRISDELLE is a registered trademark of Sebela Ireland Limited.

© 2023 Sebela Pharmaceuticals Inc. All rights reserved.

Distributed By

Padagis

Allegan, MI 49010

www.padagis.com

Rev 09-23

0S900 RC PH6

MEDICATION GUIDE

Paroxetine (pa-ROX-a-teen)

Capsules

Read the Medication Guide that comes with paroxetine capsules before you start taking it and each time you get a refill. There may be new information. This Medication Guide does not take the place of talking to your healthcare provider about your medical condition or treatment. Talk with your healthcare provider if there is something you do not understand or want to learn more about. Paroxetine capsules contain a lower dose of paroxetine, a medicine also used to treat a number of psychiatric disorders. The lower dose of paroxetine in paroxetine capsules has not been studied in any psychiatric conditions and paroxetine capsules are not approved for any psychiatric uses.

What is the most important information I should know about paroxetine capsules?

Paroxetine Capsules may cause serious side effects.

Call your healthcare provider right away if you have any of the following symptoms, or go to the nearest emergency room:

1. Suicidal thoughts or actions:
2. Paroxetine capsules, and related antidepressant medicines, may increase suicidal thoughts or actions within the first few months of treatment.
3. Depression or other serious mental illnesses are the most important causes of suicidal thoughts or actions.
4. Watch for these changes and call your healthcare provider right away if you notice:
  - New or sudden changes in mood, behavior, actions, thoughts, or feelings, especially if severe.
  - Pay particular attention to such changes when paroxetine capsules are started.

Keep all follow-up visits with your healthcare provider and call between visits if you are worried about symptoms.

Call your healthcare provider right away or go to the nearest emergency room if you have any of the following symptoms, especially if they are new, worse, or worry you:

- attempts to commit suicide
- acting on dangerous impulses
- acting aggressive or violent
- thoughts about suicide or dying
- new or worse depression
- new or worse anxiety or panic attacks
- feeling agitated, restless, angry or irritable
- trouble sleeping
- an increase in activity or talking more than what is normal for you
- other unusual changes in behavior or mood.
2. Serotonin Syndrome. This condition can be life-threatening and may include:
- agitation (nervousness), hallucinations, coma or other changes in mental status
- coordination problems or muscle twitching (small movements of the muscles that you cannot control)
- racing heartbeat, high or low blood pressure
- sweating or fever
- nausea, vomiting, or diarrhea
- muscle rigidity
- dizziness
- flushing
- tremors
- seizures
3. Reduced effectiveness of tamoxifen. Tamoxifen (a medicine used to treat breast cancer) may not work as well if it is taken while you take paroxetine capsules. If you are taking tamoxifen, tell your healthcare provider before starting paroxetine capsules.
4. Abnormal bleeding. Paroxetine capsules may increase your risk of bleeding or bruising, especially if you take the blood thinner warfarin or non-steroidal anti-inflammatory drugs (NSAIDs) like ibuprofen, naproxen, or aspirin.
5. Visual problems.
- Eye pain
- Changes in vision
- Swelling or redness in or around the eye

Only some people are at risk for these problems. You may want to undergo an eye examination to see if you are at risk and receive preventative treatment if you are.

6. Low salt (sodium) levels in the blood. Elderly people may be at greater risk for this condition. Symptoms may include:
2. headache
3. weakness or feeling unsteady
4. confusion, problems concentrating or thinking or memory problems.
7. Bone Fractures. Women who take paroxetine capsules may have a higher risk of bone fractures. Contact your healthcare provider if you have pain in a bone.
8. Manic episodes:
7. greatly increased energy
8. severe trouble sleeping
9. racing thoughts
10. reckless behavior
11. unusually grand ideas
12. excessive happiness or irritability
13. talking more or faster than usual
9. Seizures or convulsions.
10. Restlessness. Women who take paroxetine capsules may feel an inner restlessness, agitation (nervousness), or be unable to sit still or stand still especially when they start taking paroxetine capsules. Call your healthcare provider if this happens to you.
11. Driving. Paroxetine capsules may affect your ability to make decisions, think clearly, or react quickly. Do not drive, operate heavy machinery, or do other potentially dangerous activities until you know how paroxetine capsules affect you.
12. Sexual problems (dysfunction). Taking selective serotonin reuptake inhibitors (SSRIs), including paroxetine capsules may cause symptoms of sexual problems.
Symptoms in females may include:
19. Decrease sexual drive
20. Delayed or inability to have an orgasm
Talk to your healthcare provider if you develop any changes in your sexual function or if you have any questions or concerns about sexual problems during treatment with paroxetine capsules There may be treatments your healthcare provider can suggest.

What are paroxetine capsules?

Paroxetine capsules are a prescription medicine used to reduce moderate to severe hot flashes associated with menopause. Paroxetine capsules are a selective serotonin reuptake inhibitor (SSRI). It is not a hormone. The way paroxetine capsules treats hot flashes associated with menopause is not known. Paroxetine capsules do not prevent or treat osteoporosis or dryness, itching or burning in and around the vagina.

Paroxetine capsules are not for psychiatric problems such as depression, obsessive compulsive disorder, panic disorder, generalized anxiety disorder, social anxiety disorder, and post-traumatic stress disorder. Paroxetine capsules are not for use in children.

Talk to your healthcare provider if you do not think that your hot flashes are getting better while taking paroxetine capsules.

Who should not take paroxetine capsules?

Do not take paroxetine capsules if you:

- take a Monoamine Oxidase Inhibitor (MAOI).
  Ask your healthcare provider or pharmacist if you are not sure if you take an MAOI, including the antibiotic linezolid.
  - Do not take an MAOI within 14 days of stopping paroxetine capsules unless directed to do so by your healthcare provider.
  - Do not start paroxetine capsules if you stopped taking an MAOI in the last 14 days unless directed to do so by your healthcare provider.
  - People who take paroxetine capsules close in time to an MAOI may have serious or life-threatening side effects. Get medical help right away if you have any of these symptoms:
    - high fever
    - uncontrolled muscle spasms
    - stiff muscles
    - rapid changes in heart rate or blood pressure
    - confusion
    - loss of consciousness (pass out)
- take thioridazine. Do not take thioridazine together with paroxetine capsules because this can cause serious heart rhythm problems or sudden death.
- take the antipsychotic medicine pimozide. Do not take pimozide together with paroxetine capsules because this can cause serious heart problems.
- are allergic to paroxetine or any of the ingredients in paroxetine capsules. See the end of this Medication Guide for a complete list of ingredients in paroxetine capsules.
- are pregnant. Paroxetine capsules are not for pregnant women. Paroxetine, the active ingredient in paroxetine capsules, can harm your unborn baby. Risks to your unborn baby include an increased risk of birth defects, particularly heart defects. Your baby may also have certain other serious symptoms shortly after birth.

What should I tell my healthcare provider before taking paroxetine capsules?

Before starting paroxetine capsules, tell your healthcare provider if you:

- have liver problems
- have kidney problems
- have or had seizures or convulsions
- have bipolar disorder or mania
- have low sodium levels in your blood
- have or had bleeding problems
- have glaucoma (high pressure in the eye)
- have any other medical conditions
- are breastfeeding or plan to breastfeed.

Paroxetine passes into breast milk. Talk to your healthcare provider before taking paroxetine capsules if you are breast-feeding.

Tell your healthcare provider about all the medicines that you take, including prescription and over-the-counter medicines, vitamins, and herbal supplements. Paroxetine capsules and some medicines may interact with each other, may not work as well, or may cause serious side effects when taken together.

If you take paroxetine capsules, you should not take any other medicines that contain paroxetine, including Paxil, Paxil CR and Pexeva.

Especially tell your healthcare provider if you take:

- triptans used to treat migraine headache
- medicines used to treat mood, anxiety, psychotic or thought disorders, including MAOIs, SSRIs, tricyclics, lithium, buspirone, or antipsychotics
- tramadol, fentanyl, meperidine, methadone, or other opioids
- over-the-counter supplements such as tryptophan or St. John’s Wort
- amphetamines
- thioridazine
- pimozide
- tamoxifen
- atomoxetine
- cimetidine
- digoxin
- theophylline
- medicines to treat irregular heart rate (like propafenone, flecainide, and encainide)
- medicines used to treat schizophrenia
- certain medicines used to treat HIV infection
- the blood thinner warfarin
- nonsteroidal anti-inflammatory drugs (NSAIDs) (like ibuprofen, naproxen, or aspirin)
- certain medicines used to treat seizures (like phenobarbital and phenytoin)
- other drugs containing paroxetine, the medicine in paroxetine capsules.

Ask your healthcare provider if you are not sure if you are taking any of these medications.

Your healthcare provider or pharmacist can tell you if it is safe to take paroxetine capsules with your other medicines. Do not start or stop any medicine while taking paroxetine capsules without talking to your healthcare provider first.

How should I take paroxetine capsules?

- Take paroxetine capsules exactly as your healthcare provider tells you to take it.
- Take paroxetine capsules 1 time each day at bedtime.
- Paroxetine capsules may be taken with or without food.
- If you miss a dose of paroxetine capsules, take the missed dose as soon as you remember. If it is almost time for the next dose, skip the missed dose and take your next dose at the regular time. Do not take two doses of paroxetine capsules at the same time.
- If you take too much paroxetine capsules, call your healthcare provider or poison control center right away, or go to the nearest emergency room right away.

What should I avoid while taking paroxetine capsules?

- Paroxetine capsules can cause sleepiness or may affect your ability to make decisions, think clearly, or react quickly. You should not drive, operate heavy machinery, or do other dangerous activities until you know how paroxetine capsules affect you.

What are the possible side effects of paroxetine capsules?

Paroxetine capsules may cause serious side effects, including:

- See “What is the most important information I should know about paroxetine capsules?”

The most common side effects of paroxetine capsules include:

- headache
- tiredness
- nausea and vomiting

Tell your healthcare provider if you have any side effect that bothers you or does not go away. These are not all the possible side effects of paroxetine capsules. For more information, ask your healthcare provider or pharmacist.

Call your doctor for medical advice about side effects.

You may report side effects to FDA at 1-800-FDA-1088.

How should I store paroxetine capsules?

- Store paroxetine capsules at room temperature between 68°F to 77°F (20°C to 25°C).
- Keep paroxetine capsules out of the light.
- Keep paroxetine capsules dry.
- Keep paroxetine capsules and all medicines out of the reach of children.

General information about the safe and effective use of paroxetine capsules.

Medicines are sometimes prescribed for purposes other than those listed in a Medication Guide. Do not use paroxetine capsules for a condition for which it was not prescribed.

Do not give paroxetine capsules to other people, even if they have the same condition. It may harm them.

This Medication Guide summarizes the most important information about paroxetine capsules. If you would like more information, talk with your healthcare provider. You may ask your healthcare provider or pharmacist for information about paroxetine capsules that is written for healthcare professionals.

For more information about paroxetine capsules call 1-866-634-9120 or go to www.padagis.com.

What are the ingredients in paroxetine capsules?

Active ingredient: paroxetine

Inactive ingredients: dibasic calcium phosphate, sodium starch glycolate, magnesium stearate, gelatin, titanium dioxide, FD&C Yellow #6, FD&C Red #3, FD&C Red #40, shellac and black iron oxide.

This Medication Guide has been approved by the U.S. Food and Drug Administration.

Distributed By Padagis

Allegan, MI 49010 • www.padagis.com

Revised September 2023

PACKAGE/LABEL PRINCIPAL DISPLAY PANEL

NDC 0574-0279-30

Rx Only

Paroxetine Capsules

7.5 mg per capsule

30 CAPSULES